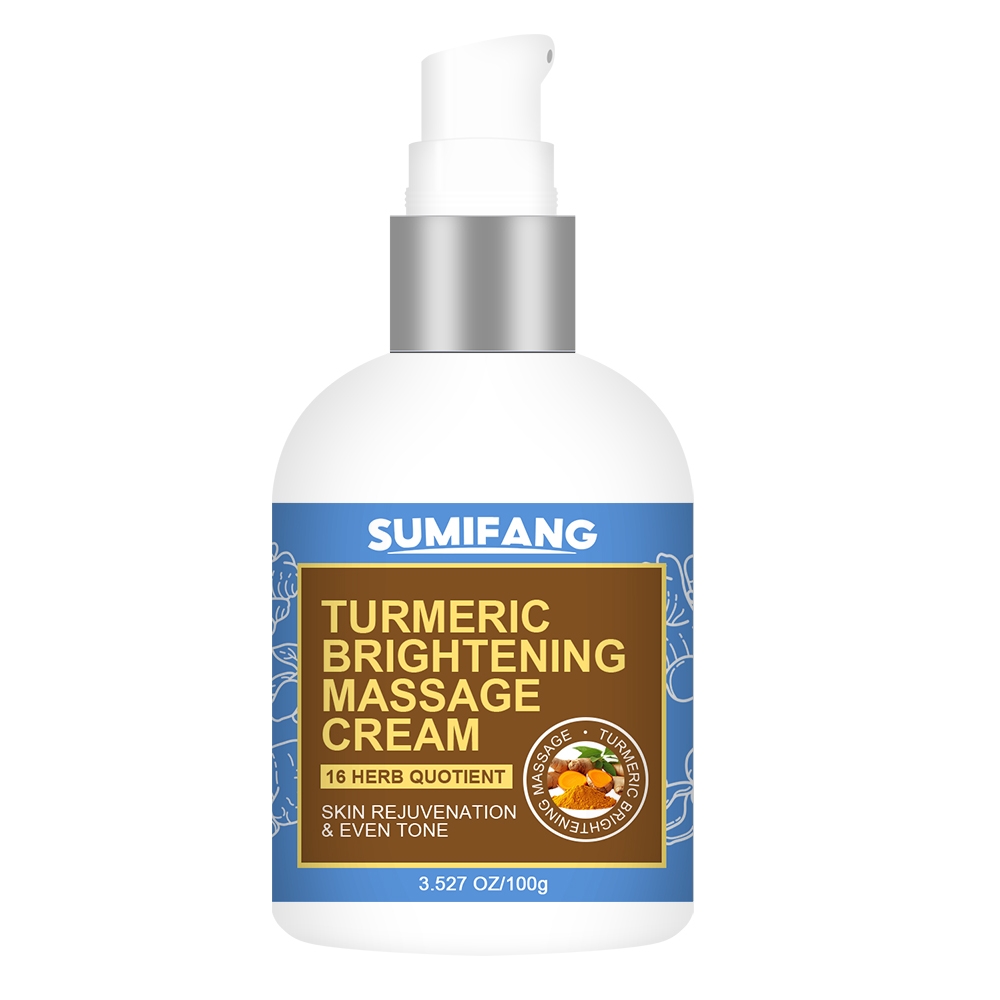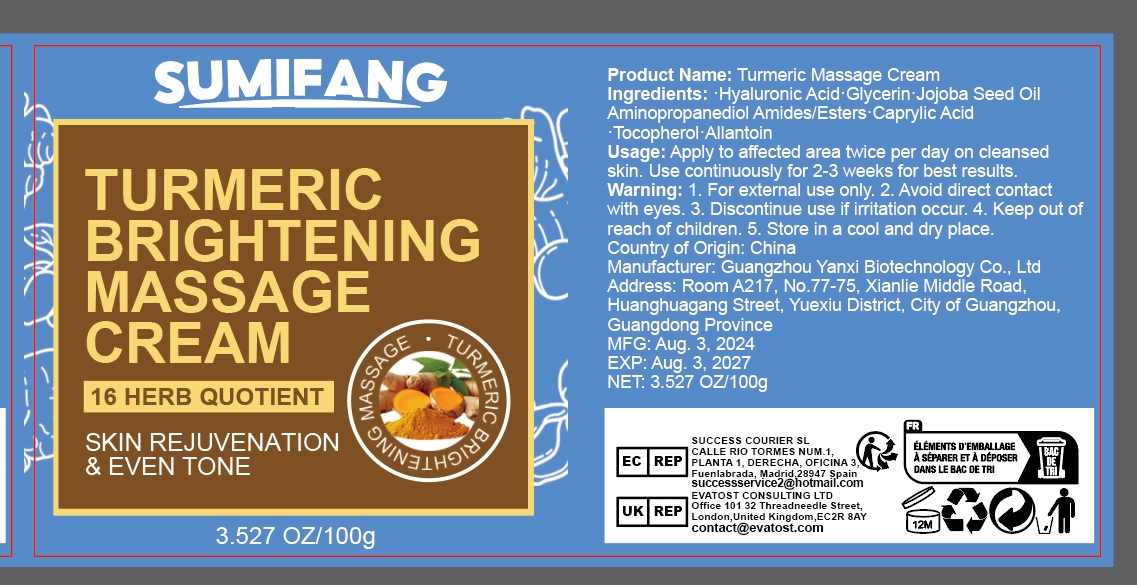 DRUG LABEL: TURMERIC BRIGHTENING MASSAGECREAM
NDC: 84025-117 | Form: CREAM
Manufacturer: Guangzhou Yanxi Biotechnology Co.. Ltd
Category: otc | Type: HUMAN OTC DRUG LABEL
Date: 20240805

ACTIVE INGREDIENTS: HYALURONIC ACID 5 mg/100 g; GLYCERIN 3 mg/100 g
INACTIVE INGREDIENTS: WATER

DOSAGE AND ADMINISTRATION

Cream for the care and massage of the body skin

WARNINGS

Keep out of children

INACTIVE INGREDIENT

Aqua

INDICATIONS AND USAGE

For daily skin care

Keep out of children

PURPOSE

Smooths and moisturizes the skin，Keeps skin glowing.